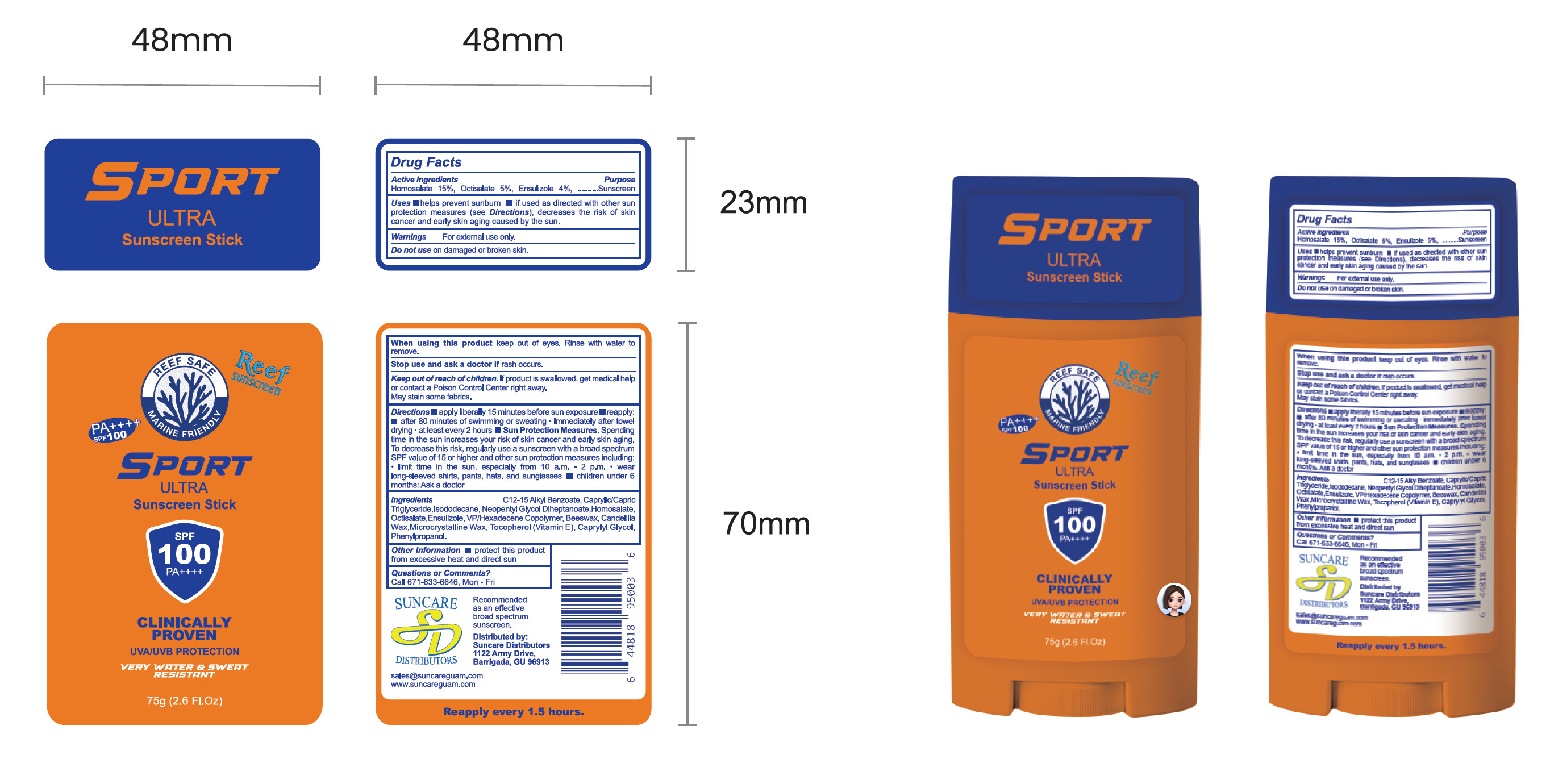 DRUG LABEL: Sunscreen Stick
NDC: 84938-015 | Form: STICK
Manufacturer: Foshan Sugar Max Cosmetics CO.,Ltd
Category: otc | Type: HUMAN OTC DRUG LABEL
Date: 20251218

ACTIVE INGREDIENTS: OCTISALATE 0.06 g/1 g; ENSULIZOLE 0.05 g/1 g; HOMOSALATE 0.15 g/1 g
INACTIVE INGREDIENTS: C12-15 ALKYL BENZOATE; CAPRYLIC/CAPRIC TRIGLYCERIDE; NEOPENTYL GLYCOL DIHEPTANOATE; BEESWAX; MICROCRYSTALLINE WAX; PHENYLPROPANOL; VP/HEXADECENE COPOLYMER; CANDELILLA WAX; ISODODECANE; TOCOPHEROL; CAPRYLYL GLYCOL

84938-015 SUNSCREEN STICK

ACTIVE INGREDIENT

Homosalate 15%,0ctisalate 5%,Ensulizole 4%

PURPOSE

Sunscreen

INDICATIONS AND USAGE

Uses helps prevent sunbum if used as directed with other sun protection measures(see Directions), decreases the risk of skin cancer and early skin aging caused by the sun.

WARNINGS

For externall use only.

Do not use on damaged or broken skin.

When using this product keep out of eyes. Rinse with water to remove.

Stop use and ask a doctor if rash occurs.

KEEP OUT OF REACH OF CHILDREN

Keep out ofreach ofchildren. lf product is swallowed, get medical help or contact a Poison Control Center right away.
May stain some fabrics.

DOSAGE AND ADMINISTRATION

Directions apply liberally 15 minutes before sun exposure m reapply: after 80 minutes of swimming or sweating lmmediately after towel drying -at least every 2 hours Sun Protection Measures.Spending time in the sun increases your risk of skin cancer and early skin aging.To decrease this risk, regularly use a sunscreen with a broad spectrum SPF value of 15 or higher and other sun protection measures including. limit time in the sun,especially from 10 a.m.-2 p.m. wearlong-sleeved shirts, pants, hats, and sunglasses
children under 6 months: Ask a doctor

INACTIVE INGREDIENT

C12‑15 Alkyl Benzoate
Caprylic/Capric Triglyceride
Isododecane
Neopentyl Glycol Diheptanoate
VP/Hexadecene Copolymer
Beeswax
Candelilla Wax
Microcrystalline Wax
Tocopherol (Vitamin E)
Caprylyl Glycol
Phenylpropanol